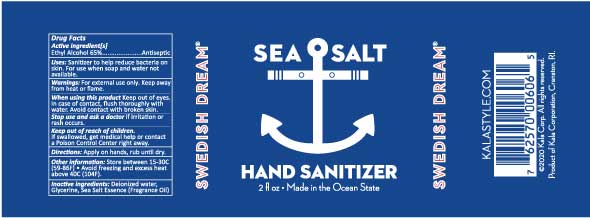 DRUG LABEL: Swedish Dream Sea Salt Hand Sanitizer
NDC: 79655-606 | Form: LIQUID
Manufacturer: Kala Corporation
Category: otc | Type: HUMAN OTC DRUG LABEL
Date: 20220113

ACTIVE INGREDIENTS: ALCOHOL 38.35 mL/59 mL
INACTIVE INGREDIENTS: LINALOOL, (+/-)- 0.05 mL/59 mL; WATER 18.88 mL/59 mL; PHENYLETHYL ALCOHOL 0.05 mL/59 mL; 3-(3,4-METHYLENEDIOXYPHENYL)-2-METHYLPROPANAL 0.05 mL/59 mL; LINALYL ACETATE 0.04 mL/59 mL; ABIES SIBIRICA LEAF OIL 0.01 mL/59 mL; .ALPHA.-AMYLCINNAMALDEHYDE DIMETHYL ACETAL 0.03 mL/59 mL; METHYL BENZODIOXEPINONE 0.05 mL/59 mL; 8-(N-INDOLYL)-2,6-DIMETHYL-7-OCTEN-2-OL 0.1 mL/59 mL; HYDROXYCITRONELLAL 0.05 mL/59 mL; CYCLAMEN ALDEHYDE 0.05 mL/59 mL; 2,6,10-TRIMETHYL-9-UNDECENAL 0.05 mL/59 mL; 2-METHYLUNDECANAL 0.05 mL/59 mL; 2-ISOBUTYL-4-METHYLTETRAHYDROPYRAN-4-OL 0.05 mL/59 mL; GLYCERIN 0.885 mL/59 mL; ETHYLENE BRASSYLATE 0.05 mL/59 mL; .ALPHA.-TERPINEOL 0.05 mL/59 mL; BENZYL SALICYLATE 0.05 mL/59 mL; ISOAMYL SALICYLATE 0.05 mL/59 mL; 3-HEXENYL SALICYLATE, CIS- 0.05 mL/59 mL; METHYL 2-NONYNOATE 0.005 mL/59 mL

Swedish Dream® Sea Salt Hand Sanitizer

Active Ingredient

Ethyl Alcohol 65%

Purpose

Antiseptic

Uses

Sanitizer to help reduce bacteria on skin. For use when soap and water not available.

Warnings

For external use only. Keep away from heat or flame.

When using this product

Keep out of eyes. In case of contact, flush thoroughly with water.

Keep out of reach of children

If swallowed get medical help or contact a poison control center right away.

Directions:

Apply on hands and rub until dry.

Other Information

Store between 15-30C(59-86F) - Avoid freezing and excess heat over 40C(104F)

Inactive Ingredients

Deionized Water, Glycerine, Sea Salt Essence (Fragrance Oil)